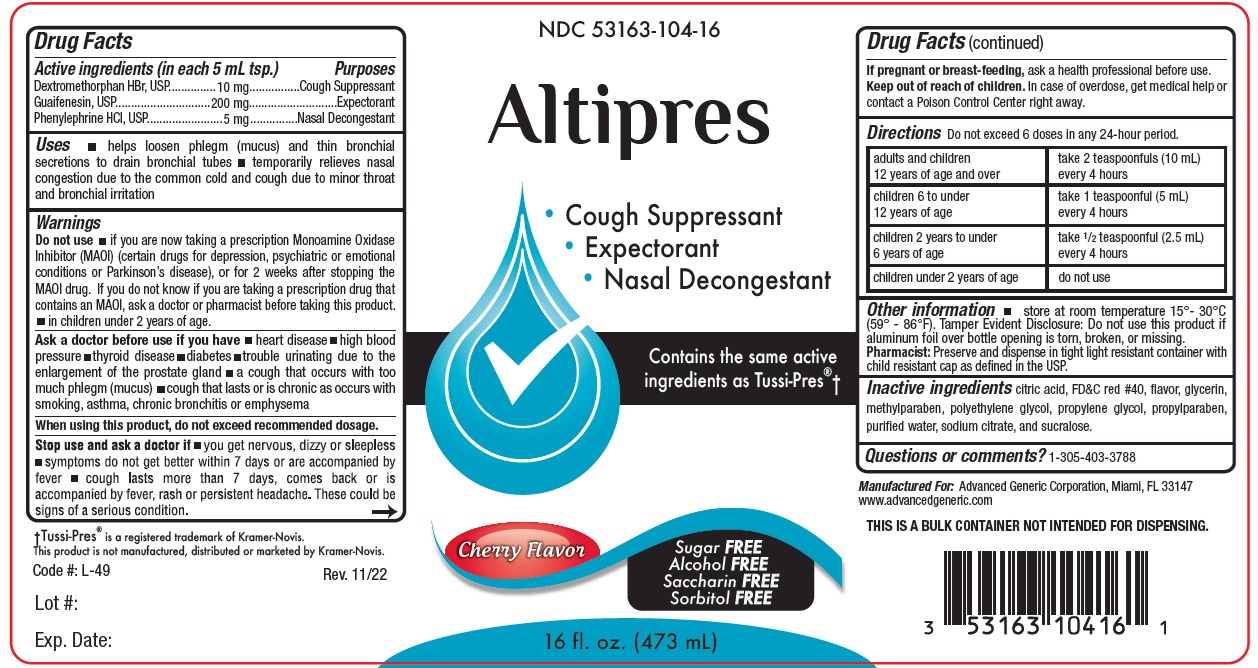 DRUG LABEL: Altipres
NDC: 53163-104 | Form: LIQUID
Manufacturer: Alternative Pharmacal Corporation
Category: otc | Type: HUMAN OTC DRUG LABEL
Date: 20251230

ACTIVE INGREDIENTS: DEXTROMETHORPHAN HYDROBROMIDE 10 mg/5 mL; GUAIFENESIN 200 mg/5 mL; PHENYLEPHRINE HYDROCHLORIDE 5 mg/5 mL
INACTIVE INGREDIENTS: SUCRALOSE; CITRIC ACID MONOHYDRATE; FD&C RED NO. 40; GLYCERIN; METHYLPARABEN; POLYETHYLENE GLYCOL, UNSPECIFIED; PROPYLPARABEN; WATER; SODIUM CITRATE; PROPYLENE GLYCOL

Alt-Altipres 104

Active Ingredients (in each 5 mL tsp.) Purpose

Dextromethorphan HBr ............... 10 mg ................ Cough Suppressant

Guaifenesin .............................. 200 mg ................ Expectorant

Phenylephrine HCl ..................... 5 mg ................... Nasal Decongestant

Purpose

Cough Suppressant

Expectorant

Nasal Decongestant

Warnings

Ask a doctor before use if you have

- heart disease
- high blood pressure
- thyroid disease
- diabetes
- trouble urinating due to the enlargement of the prostate gland
- a cough that occurs with too much phlegm (mucus)
- cough that lasts or is chronic as occurs with smoking, asthma, chronic bronchitis or emphysema

When using this product, do not exceed recommended dosage
Stop use and ask doctor if

- you get nervous, dizzy or sleepless
- symptoms do not get better within 7 days or are accompanied by fever
- cough lasts more than 7 days, comes back or is accompanied by fever, rash or persistent headache. These could be signs of a serious condition

Do not use

- if you are now taking a prescription Monoamine Oxidase Inhibitor (MAOI) (certain drugs for depression, psychiatric or emotional conditions or Parkinson's disease), or for 2 weeks after stopping the MAOI drug. If you do not know if you are taking a prescription drug that contains an MAOI; ask a doctor or pharmacist before taking this product -Do not use- in a child under 2 years of age

PREGNANCY OR BREAST FEEDING

If pregnant or breast-feeding,ask a health professional before use.

Keep out of reach of children.In case of overdose, get medical help or contact a Poison Control Center right away.

Uses

- helps loosen phlegm (mucus) and thin bronchial secretions to drain bronchial tubes
- temporarily relieves nasal congestion due to the common cold and cough due to minor throat and bronchial irritation

DOSAGE AND ADMINISTRATION

Directions Do not exceed more than 6 doses in any 24-hour period

adults and children 12 years of age and over | take 2 teaspoonfuls (10 mL) every 4 hours
children 6 to under 12 years of age | take 1 teaspoonful (5 mL) every 4 hours
children 2 years to under 6 years of age | take 1/2 teaspoonful (2.5 mL) every 4 hours
children under 2 years of age | ask a doctor

INACTIVE INGREDIENT

Inactive ingredients citric acid, flavor, FD&C Red #40, flavor, glycerin, methylparaben, polyethylene glycol, propylene glycol, propylparaben, purified water, sodium citrate and sucralose

Questions or comments?1-305-403-3788